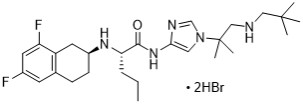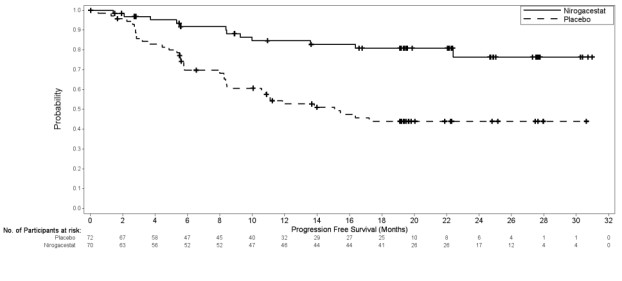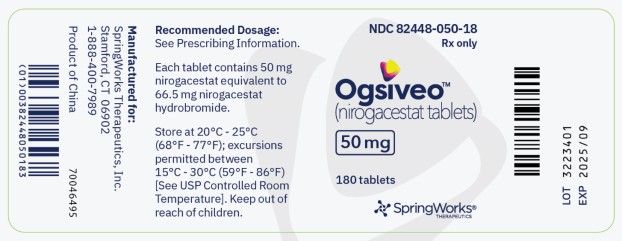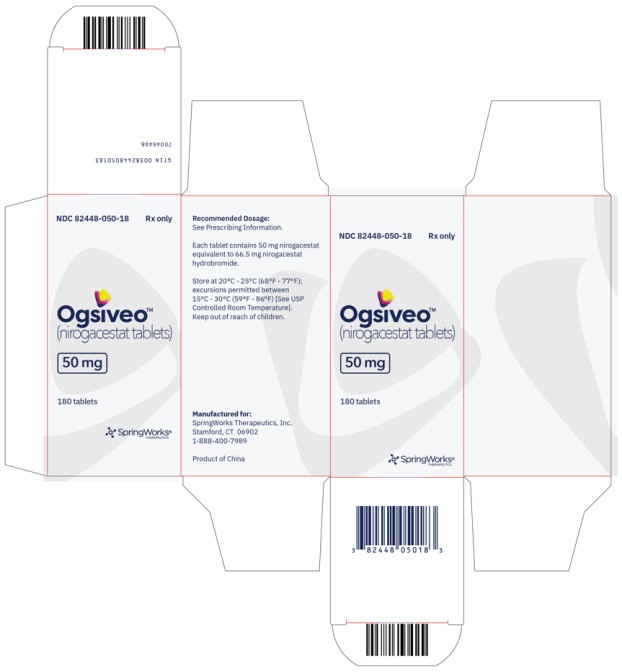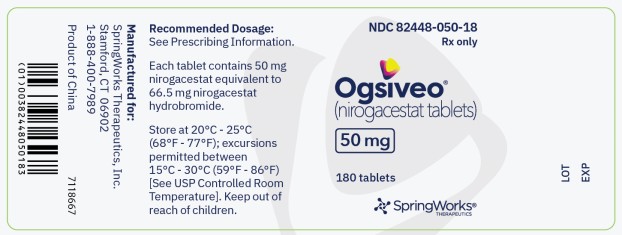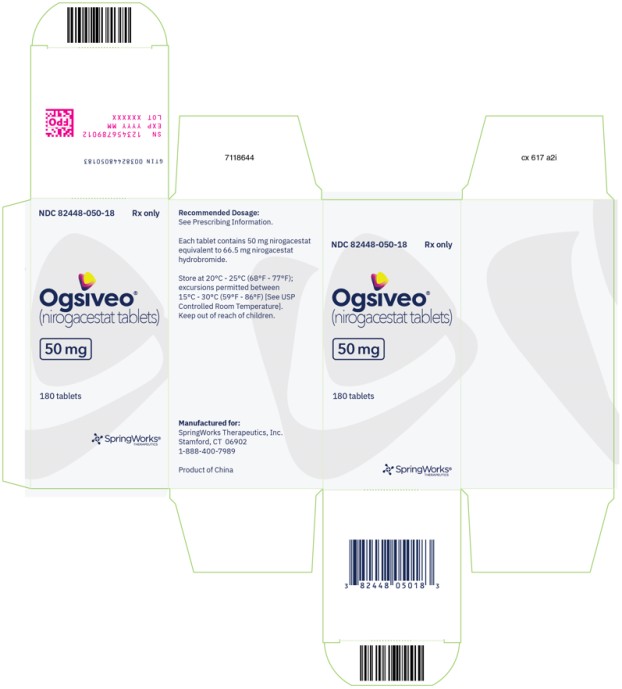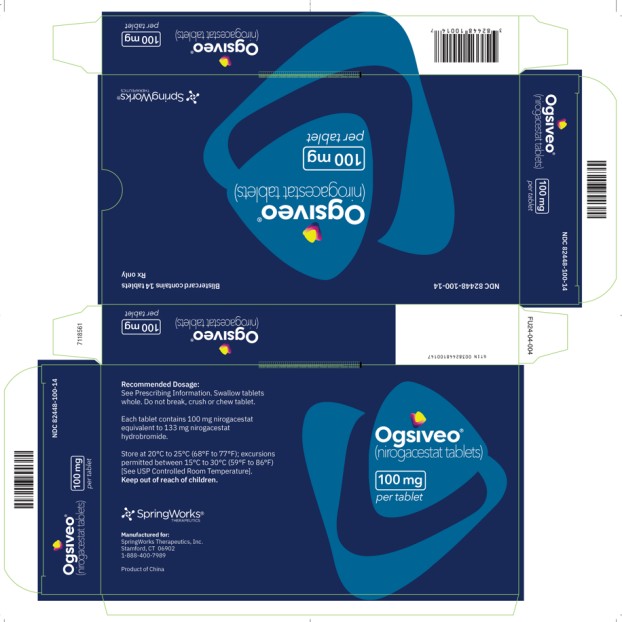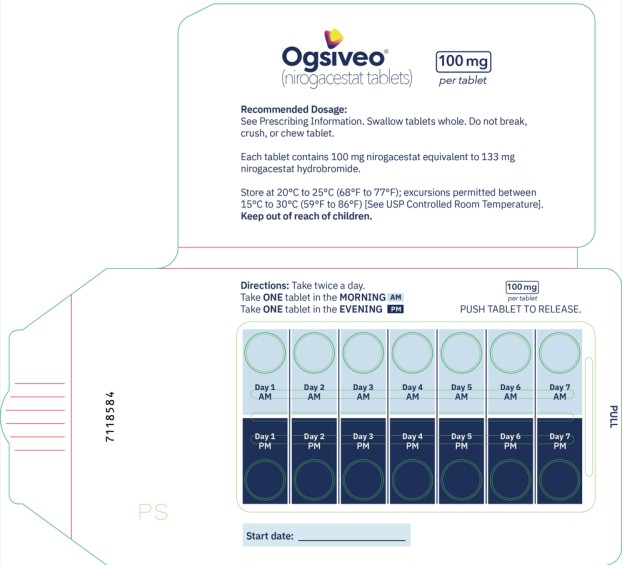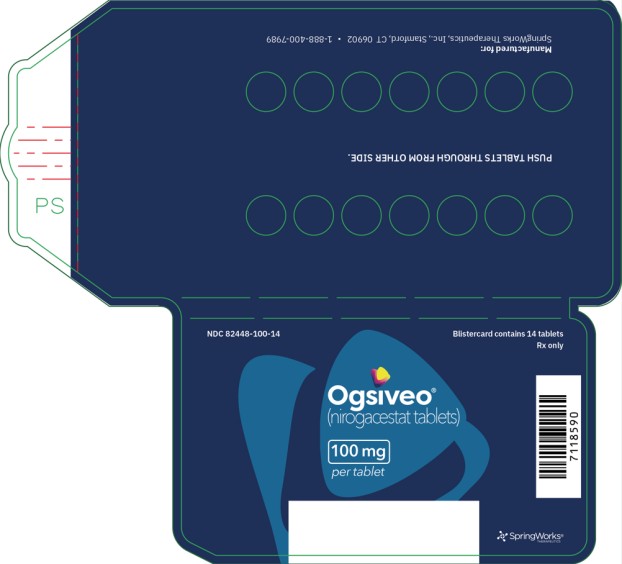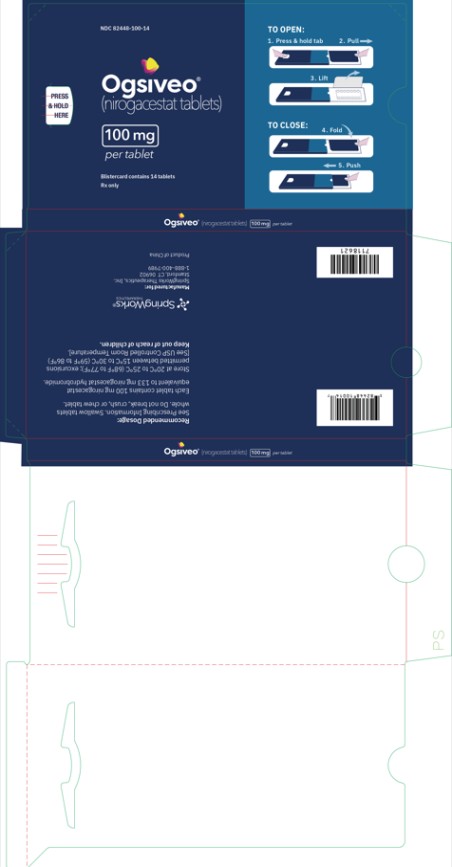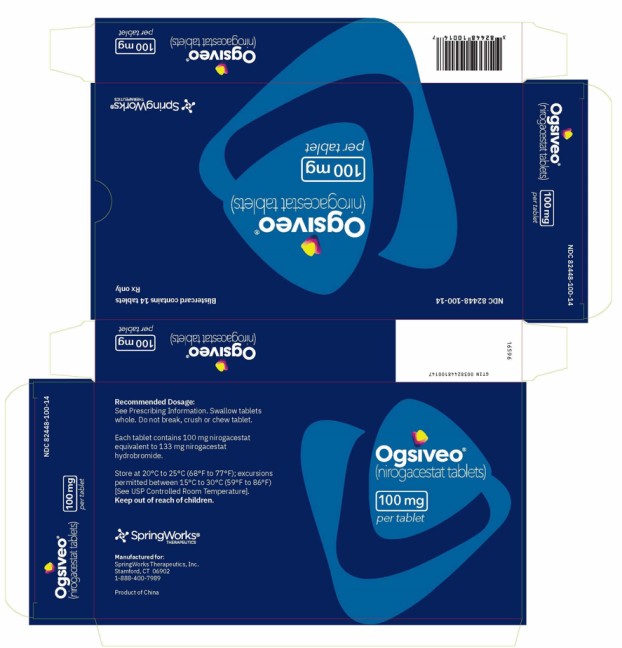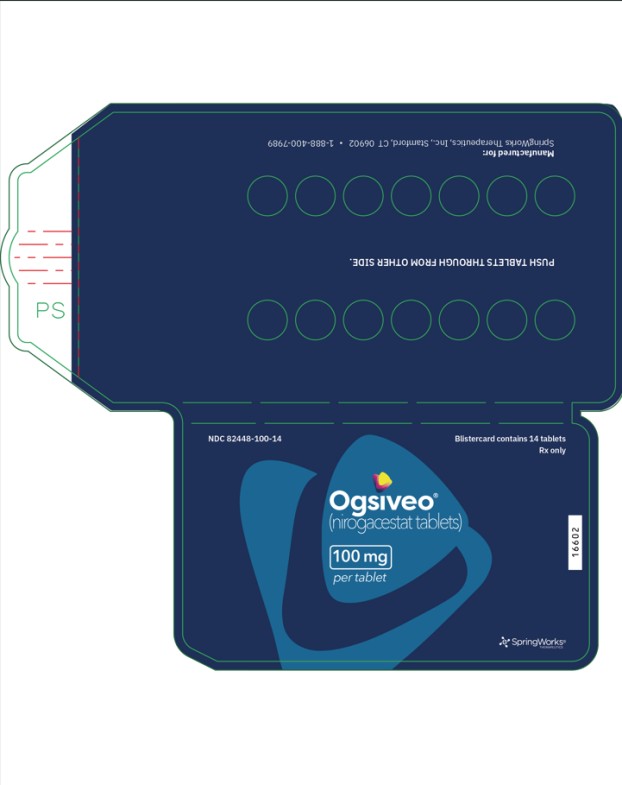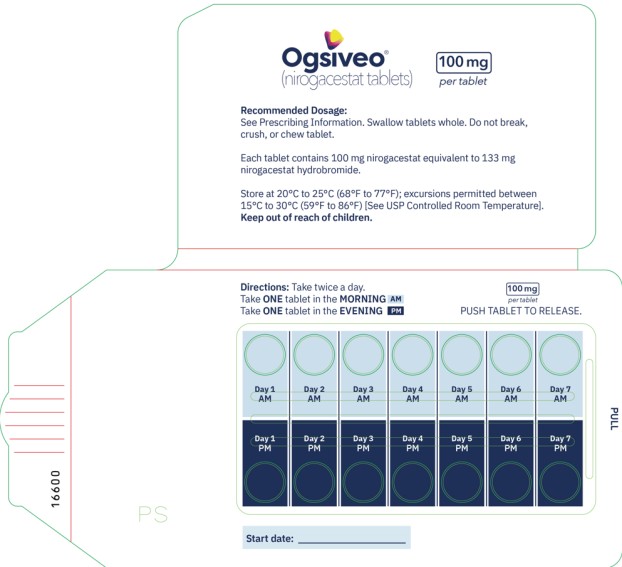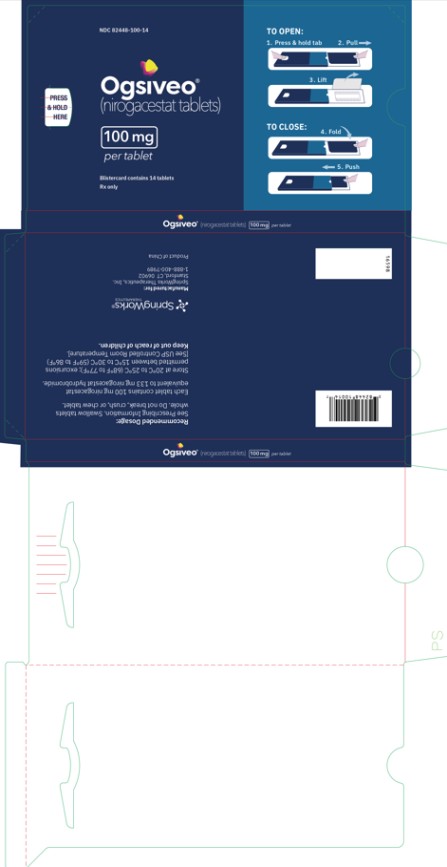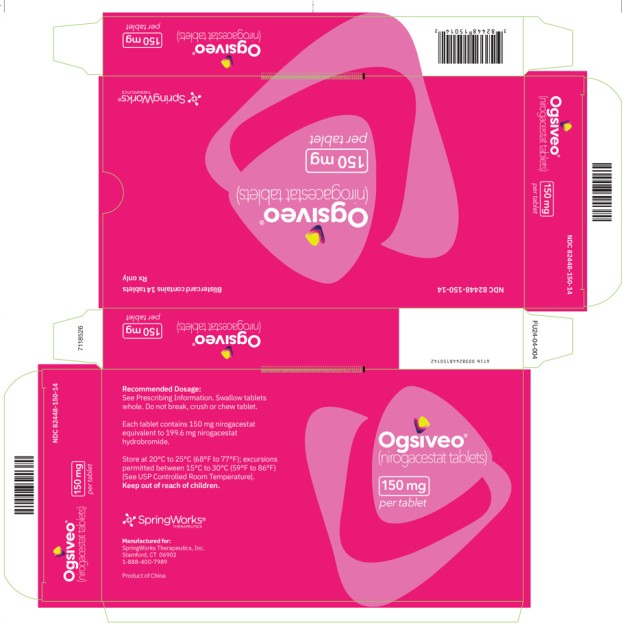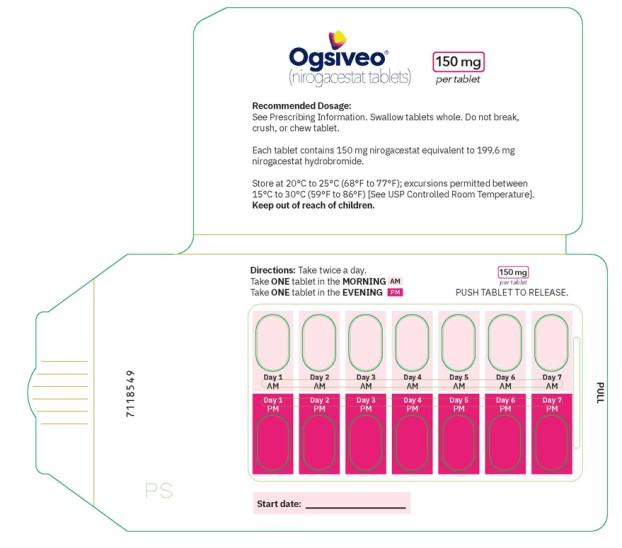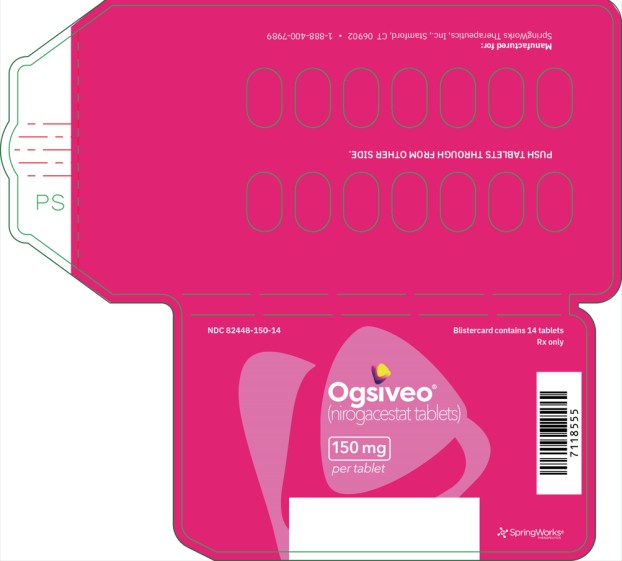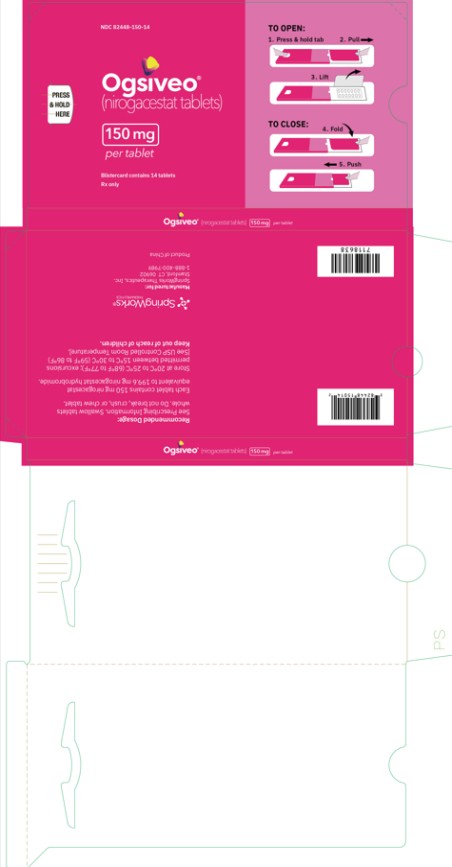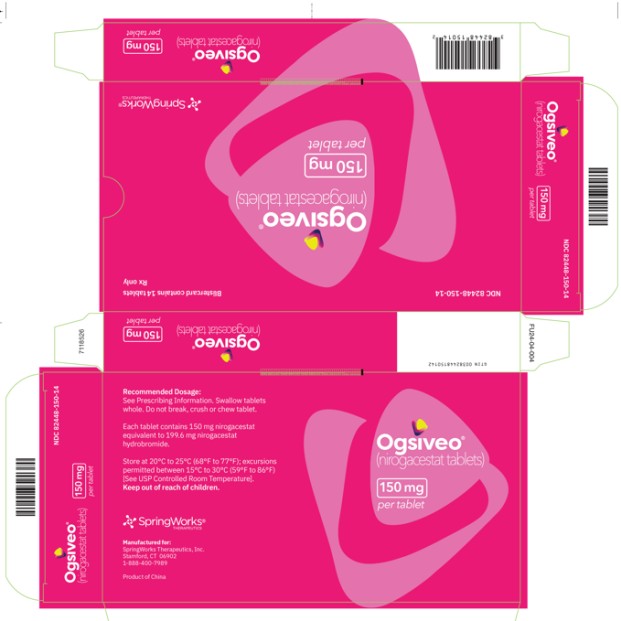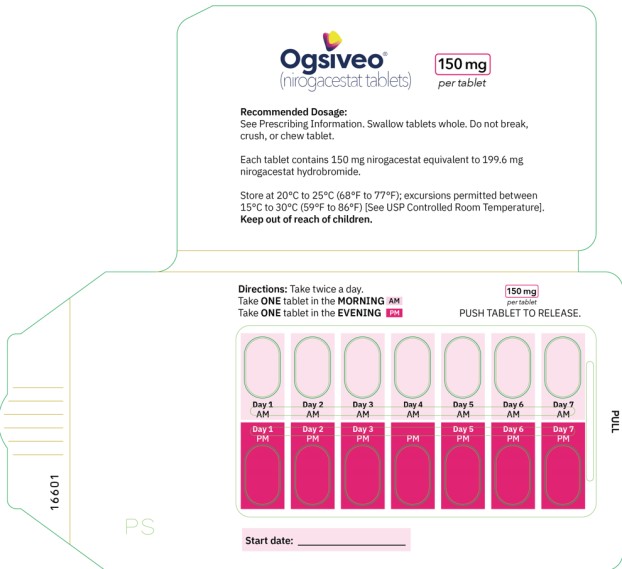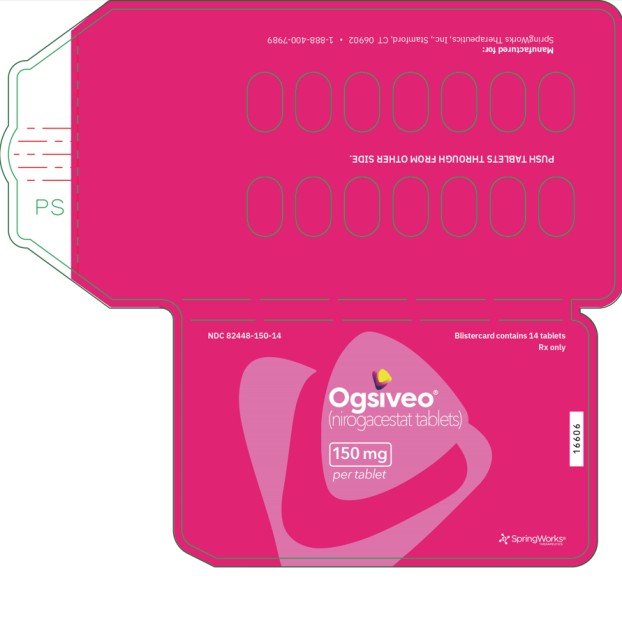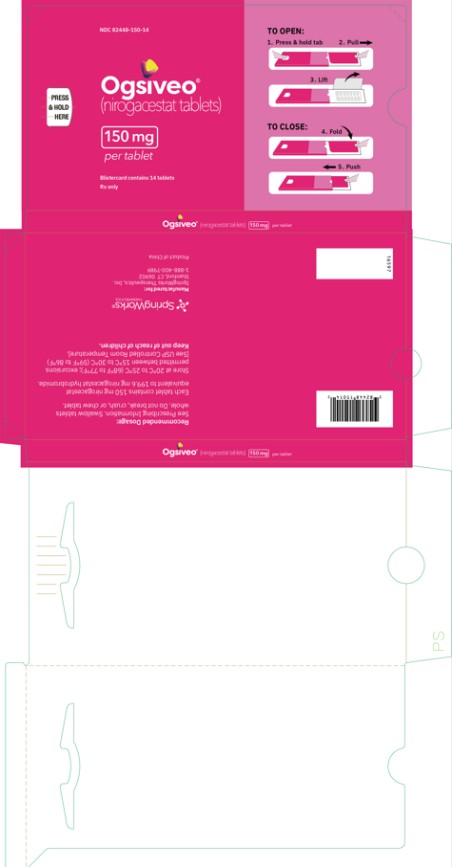 DRUG LABEL: OGSIVEO
NDC: 82448-050 | Form: TABLET, FILM COATED
Manufacturer: SpringWorks Therapeutics, Inc.
Category: prescription | Type: HUMAN PRESCRIPTION DRUG LABEL
Date: 20251020

ACTIVE INGREDIENTS: NIROGACESTAT 50 mg/1 1
INACTIVE INGREDIENTS: LACTOSE MONOHYDRATE; MAGNESIUM STEARATE; MICROCRYSTALLINE CELLULOSE; SODIUM STARCH GLYCOLATE TYPE A; TALC; TITANIUM DIOXIDE; FD&C YELLOW NO. 6; POLYVINYL ALCOHOL, UNSPECIFIED; GLYCERYL MONOCAPRYLOCAPRATE; FERRIC OXIDE YELLOW

HIGHLIGHTS OF PRESCRIBING INFORMATION

These highlights do not include all the information needed to use OGSIVEO safely and effectively. See full prescribing information for OGSIVEO.
OGSIVEO® (nirogacestat) tablets, for oral use
Initial U.S. Approval: 2023

1 INDICATIONS AND USAGE

OGSIVEO is a gamma secretase inhibitor indicated for adult patients with progressing desmoid tumors who require systemic treatment. (1)

2 DOSAGE AND ADMINISTRATION

- The recommended dosage is 150 mg orally twice daily until disease progression or unacceptable toxicity. (2.1)
- See Full Prescribing Information for dosage modifications due to adverse reactions. (2.2)

3 DOSAGE FORMS AND STRENGTHS

Tablets: 50 mg, 100 mg, and 150 mg. (3)

4 CONTRAINDICATIONS

None. (4)

5 WARNINGS AND PRECAUTIONS

- Diarrhea: Severe diarrhea can occur. Monitor and dose modify for Grade 3-4 diarrhea. (5.1)
- Ovarian Toxicity: Female reproductive function and fertility may be impaired. Advise females of reproductive potential of the potential risk prior to treatment and monitor routinely. (5.2)
- Hepatotoxicity: Elevated AST and ALT can occur. Monitor AST and ALT regularly and modify dose as recommended. (5.3)
- Non-Melanoma Skin Cancers: Perform dermatologic examination prior to initiation of OGSIVEO and routinely during treatment. (5.4)
- Electrolyte Abnormalities: Monitor phosphate and potassium regularly and modify dose as recommended. (5.5)
- Embryo-Fetal Toxicity: Can cause fetal harm. Advise patients of reproductive potential of the potential risk to a fetus and to use effective contraception. (5.6, 8.1, 8.3)

6 ADVERSE REACTIONS

The most common (> 15 %) adverse reactions are diarrhea, ovarian toxicity, rash, nausea, fatigue, stomatitis, headache, abdominal pain, cough, alopecia, upper respiratory tract infection and dyspnea. (6.1)

The most common laboratory abnormalities (≥15%) are decreased phosphate, increased urine glucose, increased urine protein, increased AST, increased ALT, and decreased potassium. (6.1)

To report SUSPECTED ADVERSE REACTIONS, contact SpringWorks Therapeutics at 1-888-400-7989 or FDA at 1-800-FDA-1088 or www.fda.gov/medwatch.

7 DRUG INTERACTIONS

- Strong or moderate CYP3A inhibitors: Avoid concomitant use. (7.1)
- Strong or moderate CYP3A inducers: Avoid concomitant use. (7.1)
- Gastric acid reducing agents: Avoid concomitant use with proton pump inhibitors and H2-receptor antagonists. If concomitant use cannot be avoided, OGSIVEO administration can be staggered with antacids. (7.1)

8 USE IN SPECIFIC POPULATIONS

- Lactation: Advise not to breastfeed. (8.2)

FULL PRESCRIBING INFORMATION

1 INDICATIONS AND USAGE

OGSIVEO is indicated for adult patients with progressing desmoid tumors who require systemic treatment.

2 DOSAGE AND ADMINISTRATION

2.1 Recommended Dosage

The recommended dosage of OGSIVEO is 150 mg administered orally twice daily until disease progression or unacceptable toxicity. Each 150 mg dose of OGSIVEO consists of three 50 mg tablets or one 150 mg tablet. OGSIVEO may be taken with or without food.

Instruct patients to swallow OGSIVEO tablets whole and not to break, crush, or chew prior to swallowing.

If a patient vomits or misses a dose, instruct the patient to take the next dose at its scheduled time.

2.2 Dosage Modifications for Adverse Reactions

The recommended dose modifications for OGSIVEO for selected severe adverse reactions are summarized in Table 1 [see Warnings and Precautions (5), Adverse Reactions (6)]. For other severe adverse reactions, life-threatening adverse reactions, or persistent intolerable Grade 2 adverse events, withhold drug until resolved to Grade ≤ 1 or baseline. Only restart at a dose of 100 mg twice daily after considering the potential benefit and likelihood of recurrence of the adverse reaction. Permanently discontinue OGSIVEO for recurrence of severe or life-threatening adverse reaction upon rechallenge at the reduced dose.

Table 1. Recommended Dose Modifications for Adverse Reactions
Adverse Reaction | Severity | OGSIVEO Dosage Modifications
Diarrhea persisting for ≥ 3 days despite maximal medical therapy [see Warnings and Precautions (5.1)] | Grades 3 or 4 | Withhold OGSIVEO until resolved to Grade ≤ 1 or baseline, then restart at a dose of 100 mg twice daily.
ALT or AST increased [see Warnings and Precautions (5.3)] | Grade 2 (≥ 3 to 5 × ULN) | Withhold OGSIVEO until ALT, AST, or both are resolved to < 3 × ULN or baseline, then restart at a dose of 100 mg twice daily.
 | Grades 3 or 4 (> 5 × ULN) | Permanently discontinue.
Hypophosphatemia persisting for ≥ 3 days despite maximal replacement therapy [see Warnings and Precautions (5.5)] | Grades 3 or 4 | Withhold OGSIVEO until resolved to Grade ≤ 1 or baseline, then restart at a dose of 100 mg twice daily.
Hypokalemia despite maximal replacement therapy [see Warnings and Precautions (5.5)] | Grades 3 or 4 | Withhold OGSIVEO until resolved to Grade ≤ 1 or baseline, then restart at a dose of 100 mg twice daily.

3 DOSAGE FORMS AND STRENGTHS

The 50 mg tablets are round, orange, film-coated, and debossed with “50” on one face. Each 50 mg tablet contains 50 mg nirogacestat.

The 100 mg tablets are round, light orange, film-coated, and debossed with “100” on one face. Each 100 mg tablet contains 100 mg nirogacestat.

The 150 mg tablets are oval, orange yellow, film-coated, and debossed with “150” on one face. Each 150 mg tablet contains 150 mg nirogacestat

4 CONTRAINDICATIONS

None.

5 WARNINGS AND PRECAUTIONS

5.1 Diarrhea

Diarrhea, sometimes severe, can occur in patients treated with OGSIVEO [see Adverse Reactions (6.1)].

In DeFi, diarrhea occurred in 84% of patients treated with OGSIVEO, and included Grade 3 events in 16% of patients. Median time to first diarrhea event for patients treated with OGSIVEO was 9 days (range: 2 to 434 days). Monitor patients and manage using antidiarrheal medications. Modify dose as recommended [see Dosage and Administration (2.2)].

5.2 Ovarian Toxicity

Female reproductive function and fertility may be impaired in patients being treated with OGSIVEO. Impact on fertility may depend on factors including the duration of therapy and the state of gonadal function at the time of treatment. The long-term effects of OGSIVEO on fertility have not been established. Advise patients on the potential risks for ovarian toxicity before initiating treatment with OGSIVEO [see Use in Specific Populations (8.3)]. Monitor patients for changes in menstrual cycle regularity or the development of symptoms of estrogen deficiency, including hot flashes, night sweats, and vaginal dryness.

5.3 Hepatotoxicity

ALT or AST elevations occurred in 30% and 33% of patients who received OGSIVEO in DeFi, respectively. Grade 3 ALT or AST elevations (> 5 × ULN) occurred in 6% and 2.9% of patients, respectively [see Adverse Reactions (6.1)]. Monitor liver function tests regularly and modify dose as recommended [see Dosage and Administration (2.2)].

5.4 Non-Melanoma Skin Cancers

New non-melanoma skin cancers can occur in patients treated with OGSIVEO. In DeFi, cutaneous squamous cell carcinoma and basal cell carcinoma occurred in 2.9% and 1.4% of patients, respectively [see Adverse Reactions (6.1)]. Perform dermatologic evaluations prior to initiation of OGSIVEO and routinely during treatment.

5.5 Electrolyte Abnormalities

Electrolyte abnormalities can occur in patients treated with OGSIVEO. In DeFi, these included decreased phosphate (65%) and decreased potassium (22%). Phosphate <2 mg/dL occurred in 20% of patients who received OGSIVEO. Grade 3 decreased potassium occurred in 1.4% of patients [see Adverse Reactions (6.1)]. Monitor phosphate and potassium levels regularly and supplement as necessary. Modify dose as recommended [see Dosage and Administration (2.2)].

5.6 Embryo-Fetal Toxicity

Based on findings from animal studies and its mechanism of action, OGSIVEO can cause fetal harm when administered to pregnant women. Oral administration of nirogacestat to pregnant rats during the period of organogenesis resulted in embryo-fetal toxicity and death at maternal exposures below the human exposure at the recommended dose of 150 mg twice daily. Advise pregnant women of the potential risk to a fetus. Advise females and males of reproductive potential to use effective contraception during treatment with OGSIVEO and for 1 week after the last dose [see Use in Specific Populations (8.1,8.3)].

6 ADVERSE REACTIONS

The following serious adverse reactions are described elsewhere in the labeling:

- Diarrhea [see Warnings and Precautions (5.1)]
- Ovarian Toxicity [see Warnings and Precautions (5.2)]
- Hepatotoxicity [see Warnings and Precautions (5.3)]
- Non-Melanoma Skin Cancers [see Warnings and Precautions (5.4)]
- Electrolyte Abnormalities [see Warnings and Precautions (5.5)]

6.1 Clinical Trials Experience

Because clinical trials are conducted under widely varying conditions, adverse reaction rates observed in the clinical trials of a drug cannot be directly compared to rates in the clinical trials of another drug and may not reflect the rates observed in practice.

The safety of OGSIVEO was evaluated in 69 patients enrolled in DeFi with progressing desmoid tumor [see Clinical Studies (14)]. Patients received OGSIVEO 150 mg orally twice daily or placebo orally twice daily until disease progression or unacceptable toxicity. The median duration of exposure to OGSIVEO was 20.6 months (range: 0.3 to 33.6).

Serious adverse reactions occurred in 20% of patients who received OGSIVEO. Serious adverse reactions occurring in ≥ 2% of patients were ovarian toxicity (4%).

Permanent discontinuation of OGSIVEO due to an adverse reaction occurred in 20% of patients. Adverse reactions which resulted in permanent discontinuation of OGSIVEO in ≥ 2% of patients were diarrhea, ovarian toxicity, increased ALT, and increased AST.

Dosage interruptions of OGSIVEO due to an adverse reaction occurred in 51% of patients. Adverse reactions which required dosage interruption in ≥ 2% of patients included diarrhea, rash, stomatitis, hypophosphatemia, fatigue, folliculitis, nausea, and ovarian toxicity.

Dose reductions of OGSIVEO due to an adverse reaction occurred in 42% of patients. Adverse reactions which required dose reductions in ≥ 2% of patients included diarrhea, rash, stomatitis, hypophosphatemia, folliculitis, hidradenitis, and ovarian toxicity.

The most common (≥ 15% with a difference between arms of ≥ 5% compared to placebo) adverse reactions that occurred in patients receiving OGSIVEO were diarrhea, ovarian toxicity, rash, nausea, fatigue, stomatitis, headache, abdominal pain, cough, alopecia, upper respiratory tract infection and dyspnea.

Table 2 summarizes the adverse reactions that occurred in DeFi.

Table 2. Adverse Reactions (≥ 15%) in Patients with Desmoid Tumor Who Received OGSIVEO with a Difference Between Arms of ≥ 5% Compared to Placebo on DeFi
Adverse Reaction | OGSIVEO (N = 69) |  | Placebo (N = 72)
 | All Grades (%) | Grade 3 (%) | All Grades (%) | Grade 3 (%)
Gastrointestinal
Diarrhea | 84 | 16 | 35 | 1.4
Nausea | 54 | 1.4 | 39 | 0
Stomatitis a | 39 | 4 | 4 | 0
Abdominal Pain a | 22 | 1.4 | 14 | 1.4
Reproductive System
Ovarian toxicity a,b | 75c | 0 | 0 | 0
Skin and Subcutaneous Tissue
Rash a | 68 | 6 | 14 | 0
Alopecia | 19 | 0 | 1.4 | 0
General
Fatigue a | 54 | 2.9 | 38 | 0
Nervous System
Headache a | 30 | 0 | 15 | 0
Respiratory
Cough a | 20 | 0 | 6 | 0
Dyspnea | 16 | 0 | 6 | 0
Infections
Upper respiratory tract infection a | 17 | 0 | 2.8 | 0

a Includes multiple related composite terms.

b Investigator assessment of ovarian toxicity included ovarian failure, premature menopause, amenorrhea, and menopause

c The number of females of reproductive potential in each arm is used as the denominator (OGSIVEO N = 36, Placebo N = 37)

Clinically relevant adverse reactions occurring in < 15% of patients receiving OGSIVEO in DeFi included non-melanoma skin cancers, epistaxis, hidradenitis suppurativa, folliculitis, and influenza-like illness.

Table 3 summarizes laboratory abnormalities in DeFi.

Table 3. Laboratory Abnormalities (≥15%) that Worsened from Baseline in Patients with Desmoid Tumor Who Received OGSIVEO in DeFi
Laboratory Abnormality | OGSIVEO |  | Placebo
 | All Grades (%) | Grade 3 or 4 (%) | All Grades (%) | Grade 3 or 4 (%)
Chemistry
Decreased phosphate a,b | 65 | Not Applicable | 11 | Not Applicable
Increased urine glucose c,d | 51 | Not Applicable | 0 | Not Applicable
Increased urine protein c | 40 | 0 | 25 | 0
Increased aspartate aminotransferase a | 33 | 2.9 | 18 | 1.4
Increased alanine aminotransferase a | 30 | 6 | 21 | 1.4
Decreased potassium a | 22 | 1.4 | 4.2 | 0

a The denominator used to calculate the rate was 69 for nirogacestat and 72 for placebo based on the number of patients with a baseline value and at least one post-treatment value.

b CTCAE Version 5.0 does not include numeric thresholds for grading of hypophosphatemia; all grades represent patients with lab value < Lower Limit of Normal (LLN).

c The denominator used to calculate the rate was 68 for nirogacestat and 69 for placebo based on the number of patients with a baseline value and at least one post-treatment value.

d CTCAE Version 5.0 does not include numeric thresholds for grading of increased urine glucose.

7 DRUG INTERACTIONS

7.1 Effects of Other Drugs on OGSIVEO

Table 4. Effects of Other Drugs on OGSIVEO
Strong or Moderate CYP3A Inhibitors
Clinical Effect | Nirogacestat is a CYP3A substrate. Strong or moderate CYP3A inhibitors increase nirogacestat exposure [see Clinical Pharmacology (12.3)], which may increase the risk of OGSIVEO adverse reactions.
Prevention or Management | Avoid concomitant use of OGSIVEO with strong or moderate CYP3A inhibitors including grapefruit products, Seville oranges, and starfruit.
Strong or Moderate CYP3A Inducers
Clinical Effect | Nirogacestat is a CYP3A substrate. Strong or moderate CYP3A inducers decrease serum nirogacestat exposure [see Clinical Pharmacology (12.3)], which may reduce the effectiveness of OGSIVEO.
Prevention or Management | Avoid concomitant use of OGSIVEO with strong or moderate CYP3A inducers.
Gastric Acid Reducing Agents
Clinical Effect | Nirogacestat is poorly soluble at pH ≥ 6. Gastric acid reducing agents may decrease serum nirogacestat exposure [see Clinical Pharmacology (12.3)], which may reduce the effectiveness of OGSIVEO.
Prevention or Management | Avoid concomitant use with proton pump inhibitors and H2 blockers. If concomitant use cannot be avoided, OGSIVEO can be staggered with antacids (e.g., administer OGSIVEO 2 hours before or 2 hours after antacid use).

7.2 Effects of OGSIVEO on Other Drugs

Table 5. Effects of OGSIVEO on Other Drugs
Certain CYP3ASubstrates
Clinical Effect | Nirogacestat increases exposure of CYP3A substrates [see Clinical Pharmacology (12.3)], which may increase the risk of adverse reactions related to these substrates.
Prevention or Management | Avoid concomitant use with CYP3A substrates where minimal concentration changes may lead to serious adverse reactions.
Certain CYP2C19 Substrates
Clinical Effect | Nirogacestat decreases exposure of CYP2C19 substrates [see Clinical Pharmacology (12.3)], which may decrease efficacy of these substrates.
Prevention or Management | Avoid concomitant use with OGSIVEO where decreased concentrations of CYP2C19 substrates may lead to significant decreases in efficacy of the CYP2C19 substrate unless otherwise recommended in the Prescribing Information for the CYP2C19 substrate.

8 USE IN SPECIFIC POPULATIONS

8.1 Pregnancy

Risk Summary

Based on findings from animal studies and its mechanism of action, OGSIVEO can cause fetal harm or loss of pregnancy when administered to a pregnant woman [see Clinical Pharmacology (12.1)]. Oral administration of nirogacestat to pregnant rats during the period of organogenesis resulted in embryo-fetal toxicity and embryo-fetal death at maternal exposures below the human exposure at the recommended dose of 150 mg twice daily [see Data]. There are no available data on the use of OGSIVEO in pregnant women. Advise pregnant women of the potential risk to a fetus.

In the U.S. general population, the estimated background risk of major birth defects and miscarriage in clinically recognized pregnancies is 2% to 4% and 15% to 20%, respectively.

Data

Animal Data

Daily oral administration of nirogacestat to pregnant rats during the period of organogenesis resulted in decreased fetal body weights, pre- and post-implantation loss, and fetal subcutis edema at doses ≥ 20 mg/kg/day (approximately 0.85 times the recommended dose of 150 mg twice daily based on area under the curve).

8.2 Lactation

Risk Summary

There are no data on the presence of nirogacestat or its metabolites in human milk or the effects of nirogacestat on a breastfed child or milk production. Because of the potential for serious adverse reactions in breastfed children, advise women not to breastfeed during treatment with OGSIVEO and for 1 week after the last dose.

8.3 Females and Males of Reproductive Potential

OGSIVEO can cause fetal harm when administered to a pregnant woman (see Use in Specific Populations (8.1)].

Pregnancy Testing

Verify the pregnancy status of females of reproductive potential prior to initiating OGSIVEO [see Use in Specific Populations (8.1)].

Contraception

Females

Advise females of reproductive potential to use effective contraception during treatment with OGSIVEO and for 1 week after the last dose.

Males

Advise males with female partners of reproductive potential to use effective contraception during treatment with OGSIVEO and for 1 week after the last dose.

Infertility

Based on findings in animal studies, OGSIVEO can impair female and male fertility. OGSIVEO has been shown to interfere with folliculogenesis and spermatogenesis in nonclinical studies resulting in changes that included ovarian atrophy [see Nonclinical Toxicology (13.1)].

8.4 Pediatric Use

The safety and effectiveness of OGSIVEO have not been established in pediatric patients. Epiphyseal disorder, manifesting as a widening of the epiphyseal growth plate, has been reported in pediatric patients with open growth plates treated with OGSIVEO.

8.5 Geriatric Use

Of the total number of OGSIVEO-treated patients in the DeFi study, 3 (4%) were 65 years of age and older and none were 75 years of age and older. Clinical studies of OGSIVEO did not include sufficient numbers of patients 65 years of age and older to determine whether they respond differently than younger adult patients.

10 OVERDOSAGE

Due to the high level of protein binding, OGSIVEO is not expected to be dialyzable [see Clinical Pharmacology (12.3)].

11 DESCRIPTION

OGSIVEO oral tablets contain nirogacestat (as nirogacestat hydrobromide), a gamma (ɣ) secretase inhibitor. Nirogacestat hydrobromide is chemically known as (S)-2-(((S)-6,8-Difluoro-1,2,3,4-tetrahydronaphthalen-2-yl)amino)-N-(1-(2-methyl-1-(neopentylamino)propan-2-yl)-1H-imidazol-4-yl) pentanamide dihydrobromide. The empirical formula is C27H43Br2F2N5O and the molecular weight is 651.48 g/mol. Nirogacestat hydrobromide is a white to off white powder with an aqueous solubility of 11.4 mg/mL and a pH of 4.4 in water at 25°C. Nirogacestat dihydrobromide is highly soluble at low pH, however the solubility significantly decreases at pH > 6.0. The molecule has pKa’s of 5.77 and 7.13. The structural formula for nirogacestat hydrobromide is:

OGSIVEO (nirogacestat) tablets are immediate release (IR), film-coated tablets intended for oral administration. Each 50 mg tablet contains 50 mg nirogacestat as 66.525 mg nirogacestat hydrobromide. OGSIVEO 50 mg tablets are round, biconvex with an approximate diameter of 8 mm. They are film coated, orange in color, and debossed with “50” on one face and plain on the other face. Each 100 mg tablet contains 100 mg nirogacestat as 133.050 mg nirogacestat hydrobromide. OGSIVEO 100 mg tablets are round, biconvex with an approximate diameter of 10 mm. They are film coated, light orange in color, and debossed with “100” on one face and plain on the other face. Each 150 mg tablet contains 150 mg nirogacestat as 199.574 mg nirogacestat hydrobromide. OGSIVEO 150 mg tablets are oval, biconvex with approximate dimensions of 8.5 X 17.5mm. They are film coated, orange yellow in color, and debossed with “150” on one face and plain on the other face.

OGSIVEO tablets contain the following inactive ingredients: lactose monohydrate, magnesium stearate, microcrystalline cellulose, and sodium starch glycolate type A. The tablets are finished with Opadry® QX orange film coating consisting of the following ingredients: FD&C yellow #6/sunset yellow FCF aluminum lake, glycerol monocaprylocaprate type 1/mono/diglycerides, iron oxide yellow, macrogol (PEG) polyvinyl alcohol graft copolymer, polyvinyl alcohol – partially hydrolyzed, talc, and titanium dioxide.

12 CLINICAL PHARMACOLOGY

12.1 Mechanism of Action

Nirogacestat is a gamma secretase inhibitor that blocks proteolytic activation of the Notch receptor. When dysregulated, Notch can activate pathways that contribute to tumor growth.

12.2 Pharmacodynamics

Exposure-Response Relationships

There is an exposure-response relationship between nirogacestat exposure and Grade 3 hypophosphatemia with a higher risk of Grade 3 hypophosphatemia at higher exposure.

Cardiac Electrophysiology

At the recommended dosage, a mean increase in the QTc interval > 20 ms was not observed.

12.3 Pharmacokinetics

Nirogacestat pharmacokinetic parameters in patients with desmoid tumors are summarized in Table 6.

Table 6. Pharmacokinetic Parameters and Characteristics of Nirogacestat
General Information
Steady state exposure [Mean (%CV)] | Cmax | 508 (62) ng/mL
 | AUC0-tau | 3370 (58) ng·h/mL
Time to steady-state |  | Approximately 6 days
Accumulation ratio [Median (Min, Max)] |  | 1.6 (1.3, 4.6)
Absorption
Tmax [Median (Min, Max)] |  | 1.5 (0.5, 6.5) hours
Absolute bioavailability |  | 19%
Food effect [dose-normalized GMR% (90% CI)] | Cmax | 93 % (55%, 166%)
 | AUC | 114% (76%, 171%)
Distribution
 | Serum protein binding | 99.6%
Protein Binding* | Human serum albumin | 94.6%
 | α-1 acid glycoprotein | 97.9%
Apparent volume of distribution (Vz/F) [Mean (%CV)] |  | 1430 (65) L
Elimination
Apparent Systemic Clearance (CL/F) [Mean (%CV)] |  | 45 (58) L/hr
Terminal elimination half-life (t1/2) [Mean (%CV)] |  | 23 (37) hr
Metabolism
Primary pathway |  | N-dealkylation via CYP3A4 (85%)
Secondary pathways |  | Metabolism by CYP 3A4, 2C19, 2C9, and 2D6
Excretion
Feces |  | 38%
Urine |  | 17% (<1% unchanged)
Expired air |  | 9.7%

* Protein binding values reflect results from separate assays.

Abbreviations: AUC0-tau = area under the time concentration curve to the dosing interval;

Cmax = maximum plasma concentration; Tmax = time to reach Cmax; GMR = geometric mean ratio

Specific Populations

No clinically significant differences in the pharmacokinetics of nirogacestat were observed based on age (18 to 80 years), sex, race (Asian, Black or African American, and White), or mild or moderate renal impairment (eGFR ≥41 mL/min/1.73m^2).

Effects of Hepatic Impairment

The mean AUC increased by up to 16% and the mean Cmax decreased by up to 39% in subjects with moderate hepatic impairment identified by Child-Pugh Class B or NCI-ODWG Group C criteria compared to that of subjects with normal hepatic function.

Insufficient data are available to characterize nirogacestat PK in patients with severe hepatic impairment.

Drug Interaction Studies

Clinical Studies and Model-Informed Approaches

Strong CYP3A inhibitors: Nirogacestat Cmax increased by 2.5-fold and AUC by 8.2-fold following coadministration of a single dose of OGSIVEO (100 mg) with itraconazole (a strong CYP3A inhibitor). Nirogacestat AUC is predicted to increase by 6.33-, 5.19-, and 3.46-fold following coadministration of multiple doses of OGSIVEO (150 mg BID) with itraconazole, ketoconazole and clarithromycin (strong CYP3A inhibitors), respectively.

Moderate CYP3A inhibitors: Nirogacestat AUC is predicted to increase by 2.73- and 3.18-fold following coadministration of multiple doses of OGSIVEO (150 mg BID) with erythromycin (moderate CYP3A inhibitor) and fluconazole (moderate CYP3A inhibitor), respectively.

Strong CYP3A inducers: Nirogacestat AUC is predicted to decrease by 85% following coadministration of multiple doses of OGSIVEO (150 mg BID) with rifampin (strong CYP3A inducer).

Moderate CYP3A inducers: Nirogacestat AUC is predicted to decrease by 67% following coadministration of multiple doses of OGSIVEO (150 mg BID) with efavirenz (moderate CYP3A inducer).

CYP3A substrates: Midazolam (CYP3A substrate) Cmax is predicted to increase by 1.77-fold and AUC by 2.07-fold following concomitant use with multiple doses of OGSIVEO (150 mg BID).

CYP2C19 substrates: Concomitant use of multiple doses of OGSIVEO (150 mg BID) with a drug that is a sensitive substrate of CYP2C19 decreases the plasma concentrations of these substrates.

P-gp substrates: Exposure to dabigatran (P-gp substrate) Cmax and AUC were not affected by concomitant use with nirogacestat.

Drugs that increase gastric pH: Concomitant administration of proton pump inhibitors (e.g., omeprazole), histamine type 2 (H2)-receptor antagonists (e.g., famotidine), or antacids (e.g., calcium) is expected to reduce concentrations of nirogacestat.

Other Drugs:

No clinically significant differences in nirogacestat pharmacokinetics were predicted when used concomitantly with cimetidine (weak CYP3A inhibitor).

No clinically significant differences were predicted in the pharmacokinetics of the following drugs when used concomitantly with nirogacestat: rosiglitazone (CYP2C8 substrate) or
S-warfarin (CYP2C9 substrate).

In Vitro Studies

Nirogacestat does not inhibit CYP 1A2, 2B6, 2C8, 2C9, 2C19, and 2D6.

Nirogacestat is an inducer of CYP2B6, CYP2C8, CYP2C9, and CYP2C19, but does not induce CYP 1A2.

Transporter systems: Nirogacestat is a P-gp substrate, but not a substrate of BCRP, OATP1B1, and OATP1B3.

Nirogacestat is a P-gp inhibitor, but not an inhibitor of BCRP, MATE1, MATE2-K, OATP1B1, OATP1B3, OAT1, OAT2 and OAT3.

13 NONCLINICAL TOXICOLOGY

13.1 Carcinogenesis, Mutagenesis, Impairment of Fertility

Carcinogenesis

In a 6-month carcinogenicity study, transgenic rasH2 mice received up to 100 mg/kg/day of oral nirogacestat, resulting in mean exposure levels (AUC) less than those in humans at the recommended dose of 150 mg twice daily. No statistically significant neoplastic findings occurred. The carcinogenic potential of nirogacestat in rats has not been assessed.

Mutagenesis

Nirogacestat was not mutagenic in a bacterial reverse mutation (Ames) assay and was not clastogenic in an in vitro chromosome aberration assay in human lymphocytes or in vivo rat bone marrow micronucleus study.

Impairment of Fertility

Nirogacestat resulted in reduced fertility when administered to male and female rats at doses ≥ 5 mg/kg/day (approximately 0.16 times the recommended dose of 150 mg twice daily based on body surface area (BSA), and a lack of fertility when administered to male and female rats at doses ≥ 40 mg/kg/day (approximately 1.3 times the recommended dose of 150 mg twice daily based on BSA). Adverse findings in rats included ovarian atrophy, reduced testes weights, and decreased sperm concentration and motility.

14 CLINICAL STUDIES

14.1 Desmoid Tumor

The efficacy of OGSIVEO was evaluated in DeFi (NCT03785964), an international, multicenter, randomized (1:1), double-blind, placebo-controlled trial in 142 adult patients with progressing desmoid tumors not amenable to surgery. Patients were eligible if the desmoid tumor had progressed within 12 months of screening. Patients with progressing desmoid tumor that would result in immediate risk to the patient were not eligible.

Patients were randomized to receive 150 mg OGSIVEO or placebo orally twice daily until disease progression or unacceptable toxicity. Patients were stratified by primary tumor(s) location (intra-abdominal versus extra-abdominal). Tumor imaging occurred every 3 months. Crossover was permitted at the time of radiographic progression. The major efficacy outcome was progression-free survival (PFS) based on RECIST v1.1 as assessed by blinded independent central review or on clinical progression by the investigator (and confirmed by independent review). Clinical progression required worsening of symptoms resulting in a global deterioration of health status causing the permanent discontinuation from trial treatment and the initiation of emergent treatment (e.g., radiotherapy, surgery, or systemic therapy including chemotherapy or tyrosine kinase inhibitors) for desmoid tumors. Objective response rate (ORR) was an additional efficacy outcome measure. Worst pain (item 3) was assessed daily using Brief Pain Inventory-Short Form (BPI-SF), an 11-point numerical rating scale ranging from 0 (“no pain”) to 10 (“pain as bad as you can imagine”) and averaged over 7 days prior to each visit.

A total of 142 patients were randomized. The median age was 34 years (range: 18 to 76); 65% were female; race was 83% White, 6% Black, 3% Asian, and other or not reported in 8%; and 73% had an ECOG performance status (PS) of 0, 27% had an ECOG PS of 1, and 0.7% had an ECOG PS of 2. Twenty-three percent of patients had intra-abdominal disease or both intra- and extra-abdominal disease, and 77% had only extra-abdominal disease. Forty-one percent of patients had multifocal disease and 59% had single focal disease. Of 105 patients with known tumor mutation status, 81% had a CTNNB1 mutation and 21% had an APC mutation. Seventeen percent of patients had a family history of familial adenomatous polyposis (FAP). Twenty-three percent of patients received no prior therapy, and 44% received ≥3 prior lines of therapy. Prior therapy included surgery (53%), radiotherapy (23%), and systemic therapy (61%). Thirty-three percent of patients were previously treated with a tyrosine kinase inhibitor and 36% were previously treated with chemotherapy. Fifty percent had a BPI-SF item 3 (worst pain) score of ≥2.

Efficacy results are summarized in Table 7 and Figure 1.

Table 7. Efficacy Results of DeFi
 | OGSIVEO N = 70 | Placebo N = 72
Progression-free Survival
Number (%) of patients with event | 12 (17) | 37 (51)
Radiographic progression a | 11 (16) | 30 (42)
Clinical progression a | 1 (1) | 6 (8)
Death | 0 | 1 (1)
Median (months) (95% CI) b | NR (NR, NR) | 15.1 (8.4, NR)
Hazard ratio (95% CI) | 0.29 (0.15, 0.55)
p-value c | < 0.001
Objective Response Rate a
ORR, n (%) 95% CI d | 29 (41) (29.8, 53.8) | 6 (8) (3.1, 17.3)
CR | 5 (7) | 0
PR | 24 (34) | 6 (8)
p-value e | <0.001

Abbreviations: CI: confidence interval; CR: complete response; ORR: objective response rate; PR: partial response; NR: Not Reached

a Assessed by blinded independent central review.

b Obtained using Kaplan-Meier Methodology.

c p-value was from a one-sided stratified log-rank test with placebo as reference.

d Obtained using exact method based on binomial distribution.

e p-value was from a two-sided Cochran-Mantel-Haenszel test.

Figure 1. Kaplan-Meier Curve of PFS in DeFi

PFS results were supported by change from baseline in patient-reported worst pain favoring the OGSIVEO arm.

An exploratory analysis of PFS based on only radiographic progression demonstrated a hazard ratio of 0.31 (95% CI: 0.16, 0.62).

16 HOW SUPPLIED/STORAGE AND HANDLING

OGSIVEO (nirogacestat) is supplied as 50 mg, 100 mg, and 150 mg tablets. Each 50 mg orange, film-coated tablet is debossed with a “50” on one side. Each 100 mg light orange, film-coated tablet is debossed with a “100” on one face. Each 150 mg orange yellow, film-coated tablet is debossed with a “150” on one face.

The 50 mg tablets are packaged in high density polyethylene (HDPE) bottles with child-resistant closures. Each bottle contains 180 tablets: NDC # 82448-050-18. The 100 and 150 mg tablets are packaged in 14 count blister cards with child resistant closure (100 mg - NDC #82448-100-14; 150 mg - NDC #82448-150-14).

Store at 20°C-25°C (68°F-77°F). Excursions permitted between 15°C-30°C (59°F-86°F). See USP Controlled Room Temperature.

17 PATIENT COUNSELING INFORMATION

Advise the patient to read the FDA-approved patient labeling (Patient Information).

Diarrhea

Advise patients that OGSIVEO can cause diarrhea, which may be severe, and to contact their healthcare provider for sustained diarrhea that does not respond to supportive care [see Dosage and Administration (2.2), Warnings and Precautions (5.1)].

Ovarian Toxicity

Advise females of reproductive potential that OGSIVEO can cause ovarian toxicity and impair fertility, and that these effects may continue following discontinuation of OGSIVEO. Advise patients to tell their healthcare provider if they experience symptoms of ovarian toxicity, including hot flashes or menstrual irregularities [see Warnings and Precautions (5.2)].

Liver Toxicity

Advise patients that OGSIVEO can cause ALT or AST elevations, and that their healthcare provider should monitor liver transaminase levels regularly [see Dosage and Administration (2.2), Warnings and Precautions (5.3)].

Non-Melanoma Skin Cancers

Advise patients that OGSIVEO can cause new non-melanoma skin cancers, that they will be monitored for these, and to contact their healthcare provider for any new or changing lesions on their skin [see Warnings and Precautions (5.4)].

Electrolyte Abnormalities

Advise patients that OGSIVEO can cause hypophosphatemia and/or hypokalemia which may require phosphate and/or potassium supplementation. Advise patients that they will be monitored for these and to contact their healthcare provider if they experience muscle pain or weakness [see Dosage and Administration (2.2), Warnings and Precautions (5.5)].

Embryo-Fetal Toxicity

Advise pregnant women and females of reproductive potential of the potential harm to a fetus. Advise females of reproductive potential to inform their healthcare provider of a known or suspected pregnancy, and to stop taking OGSIVEO if they become pregnant. Also, advise females of reproductive potential to use effective contraception during treatment with OGSIVEO and for 1 week after the last dose. Advise males with female partners of reproductive potential to use effective contraception during treatment with OGSIVEO and for 1 week after the last dose [see Warnings and Precautions (5.6), Use in Specific Populations (8.3)].

Lactation

Advise women not to breastfeed during treatment with OGSIVEO and for 1 week after the last dose [see Use in Specific Populations (8.2)].

Drug Interactions

Advise patients to inform their healthcare provider of all concomitant medications, including prescription medicines, over-the-counter drugs, vitamins, and herbal products. Inform patients to avoid starfruit, Seville oranges, grapefruit, and juice from any of these fruits when taking OGSIVEO [see Drug Interactions (7)].

Manufactured for:

SpringWorks Therapeutics, Inc. Stamford, CT 06902

OGSIVEO® is a trademark of SpringWorks Therapeutics, Inc.

©2024 SpringWorks Therapeutics, Inc.

PATIENT INFORMATION
OGSIVEO (og-SIH-vee-oh)
(nirogacestat)
tablets

What is OGSIVEO?
OGSIVEO is a prescription medication used to treat adults with progressing desmoid tumors who require a medicine by mouth or injection (systemic therapy).
It is not known if OGSIVEO is safe and effective in children.

Before taking OGSIVEO tell your healthcare provider about all of your medical conditions, including if you:

- have liver problems.
- are pregnant or plan to become pregnant. OGSIVEO can harm your unborn baby. Tell your healthcare provider if you become pregnant or think you may be pregnant during treatment with OGSIVEO.
  Females who are able to become pregnant:
  ○ Your healthcare provider will give you a pregnancy test before you start treatment with OGSIVEO.
  ○ You should use effective birth control (contraception) during treatment with OGSIVEO and for 1 week after the last dose. Talk to your healthcare provider about birth control methods that may be right for you.
  ○ Stop taking OGSIVEO and tell your healthcare provider right away if you become pregnant.
  ○ Males with female partners who are able to become pregnant should use effective birth control (contraception) during treatment with OGSIVEO and for 1 week after the last dose.
- are breastfeeding or plan to breastfeed. It is not known if OGSIVEO passes into your breast milk. Do not breastfeed during treatment with OGSIVEO and for 1 week after the last dose.

Tell your healthcare provider about all the medicines you take, including prescription and over-the counter medicines, vitamins, and herbal supplements.
You should avoid taking proton pump inhibitors (PPIs) and H2 blockers during treatment with OGSIVEO. Ask your healthcare provider if you are not sure if you take one of these medicines.

How should I take OGSIVEO?

- Take OGSIVEO exactly as your healthcare provider tells you to take it.
- Your healthcare provider may change your dose, temporarily stop, or permanently stop treatment with OGSIVEO if you develop side effects.
- Take OGSIVEO 2 times a day with or without food.
- Swallow OGSIVEO tablets whole. Do not break, crush or chew tablets.
- If you take an antacid medicine, take OGSIVEO 2 hours before or 2 hours after taking the antacid.
- If you vomit after taking a dose or miss a dose of OGSIVEO, take your next dose at your regular time. Do not take 2 doses of OGSIVEO to make up the dose.

What should I avoid while taking OGSIVEO?
Avoid eating or drinking grapefruit products, Seville oranges, and starfruit during treatment with OGSIVEO.

What are the possible side effects of OGSIVEO?
OGSIVEO can cause serious side effects, including:

- Diarrhea. Diarrhea is common during treatment with OGSIVEO and may sometimes be severe. Your healthcare provider may tell you to drink more fluids or may tell you to take antidiarrheal medicines. Tell your healthcare provider right away if you have diarrhea that lasts longer than a few days and does not get better after taking antidiarrheal medicines.
- Ovarian problems. Females who are able to become pregnant may have ovarian problems and changes in their menstrual cycle during treatment with OGSIVEO. OGSIVEO may affect fertility which may affect your ability to have a child. Tell your healthcare provider if you have any changes in your menstrual cycle or any hot flashes, night sweats or vaginal dryness during treatment with OGSIVEO.
- Liver problems. OGSIVEO can cause an increase in liver enzymes. Your healthcare provider will do blood tests to check your liver function before you start and during your treatment with OGSIVEO.
- New Non-Melanoma Skin Cancers. Your healthcare provider will do skin exams before and during treatment with OGSIVEO if you are at risk for skin cancer. Tell your healthcare provider if you have any new or changing skin lesions.
- Electrolyte (salt) problems. Your healthcare provider will do blood tests to check your phosphate and potassium levels during treatment with OGSIVEO and may give you medicines to treat low phosphate or low potassium if needed. Tell your healthcare provider if you develop any muscle pain or weakness.

The most common side effects of OGSIVEO are:

- rash

- stomach (abdominal) pain

- nausea

- cough

- tiredness

- hair loss

- mouth sores

- upper respiratory infection

- headache

- shortness of breath

OGSIVEO can affect fertility in females and males, which may affect your ability to have a child. Talk to your healthcare provider if this is a concern for you.
These are not all of the possible side effects of OGSIVEO.
Call your doctor for medical advice about side effects. You may report side effects to FDA at 1-800-FDA-1088.

How do I store OGSIVEO?

- Store OGSIVEO tablets at room temperature between 68°F to 77°F (20°C to 25°C).

Keep OGSIVEO and all medicines out of reach of children.

General information about safe and effective use of OGSIVEO.
Medicines are sometimes prescribed for purposes other than those listed in a Patient Information leaflet. Do not use OGSIVEO for a condition for which it is not prescribed. Do not give OGSIVEO to other people even if they have the same symptoms you have. It may harm them. You can ask your healthcare provider or pharmacist for information about OGSIVEO that is written for health professionals.

What are the ingredients in OGSIVEO?
Active ingredient: nirogacestat
Inactive ingredients: lactose monohydrate, magnesium stearate, microcrystalline cellulose, and sodium starch glycolate type A.
Film Coating ingredients: FD&C yellow #6/sunset yellow FCF aluminum lake, glycerol monocaprylocaprate type 1/mono/diglycerides, iron oxide yellow, macrogol (PEG) polyvinyl alcohol graft copolymer, polyvinyl alcohol – partially hydrolyzed, talc, and titanium dioxide.
Manufactured for SpringWorks Therapeutics, Inc.
Stamford, CT 06902.
OGSIVEO® is a trademark of SpringWorks Therapeutics, Inc.
©2024 SpringWorks Therapeutics, Inc.

PRINCIPAL DISPLAY PANEL

NDC 82448-050-18
Rx Only
Ogsiveo
50 mg
180 tablets

PRINCIPAL DISPLAY PANEL

NDC 82448-100-14
Rx Only
Ogsiveo
100 mg
per tablet

PRINCIPAL DISPLAY PANEL

Rx Only
Ogsiveo
100 mg

PRINCIPAL DISPLAY PANEL

Rx Only
Ogsiveo
100 mg
per tablet

PRINCIPAL DISPLAY PANEL

NDC 82448-150-14
Rx Only
Ogsiveo
150 mg
per tablet

PRINCIPAL DISPLAY PANEL

Ogsiveo
150 mg
per tablet